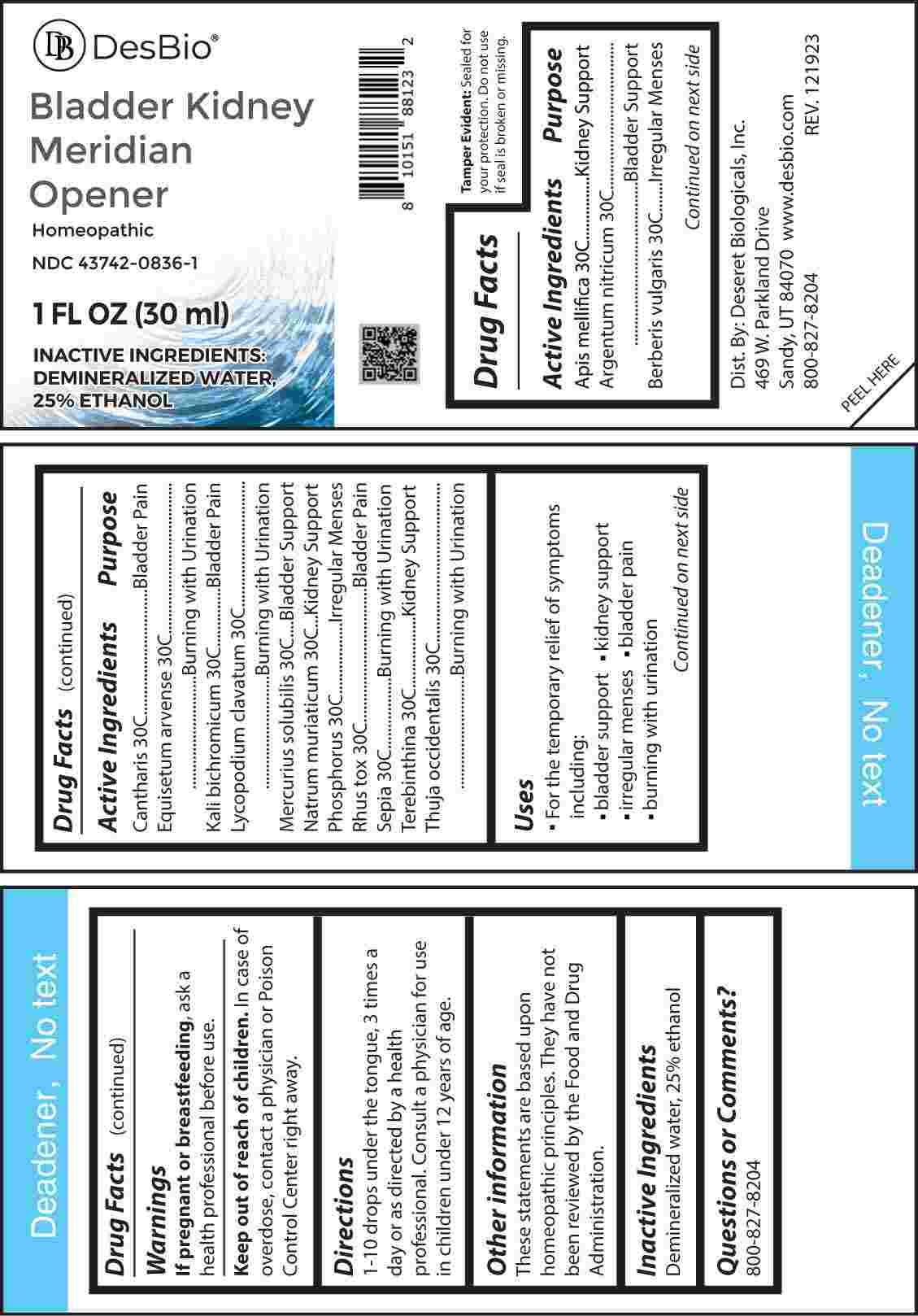 DRUG LABEL: Bladder Kidney Meridian Opener
NDC: 43742-0836 | Form: LIQUID
Manufacturer: Deseret Biologicals, Inc.
Category: homeopathic | Type: HUMAN OTC DRUG LABEL
Date: 20240315

ACTIVE INGREDIENTS: APIS MELLIFERA 30 [hp_C]/1 mL; SILVER NITRATE 30 [hp_C]/1 mL; BERBERIS VULGARIS ROOT BARK 30 [hp_C]/1 mL; LYTTA VESICATORIA 30 [hp_C]/1 mL; EQUISETUM ARVENSE TOP 30 [hp_C]/1 mL; POTASSIUM DICHROMATE 30 [hp_C]/1 mL; LYCOPODIUM CLAVATUM SPORE 30 [hp_C]/1 mL; MERCURIUS SOLUBILIS 30 [hp_C]/1 mL; SODIUM CHLORIDE 30 [hp_C]/1 mL; PHOSPHORUS 30 [hp_C]/1 mL; TOXICODENDRON PUBESCENS LEAF 30 [hp_C]/1 mL; SEPIA OFFICINALIS JUICE 30 [hp_C]/1 mL; TURPENTINE OIL 30 [hp_C]/1 mL; THUJA OCCIDENTALIS LEAF 30 [hp_C]/1 mL
INACTIVE INGREDIENTS: WATER; ALCOHOL

DRUG FACTS:

ACTIVE INGREDIENTS:

Apis Mellifica 30C, Argentum Nitricum 30C, Berberis Vulgaris 30C, Cantharis 30C, Equisetum Arvense 30C, Kali Bichromicum 30C, Lycopodium Clavatum 30C, Mercurius Solubilis 30C, Natrum Muriaticum 30C, Phosphorus 30C, Rhus Tox 30C, Sepia 30C, Terebinthina 30C, Thuja Occidentalis 30C.

PURPOSE:

Apis Mellifica – Kidney Support, Argentum Nitricum – Bladder Support, Berberis Vulgaris – Irregular Menses, Cantharis – Bladder Pain, Equisetum Arvense – Burning with Urination, Kali Bichromicum – Bladder Pain, Lycopodium Clavatum – Burning with Urination, Mercurius Solubilis – Bladder Support, Natrum Muriaticum – Kidney Support, Phosphorus – Irregular Menses, Rhus Tox – Bladder Pain, Sepia – Burning with Urination, Terebinthina – Kidney Support, Thuja Occidentalis – Burning with Urination

USES:

• For the temporary relief of symptoms including:

• bladder support • kidney support • irregular menses • bladder pain • burning with urination

These statements are based upon homeopathic practice. They have not been reviewed by the Food and Drug Administration.

WARNINGS:

If pregnant or breast-feeding, ask a health professional before use.

Keep out of reach of children. In case of overdose, contact a physician or Poison Control Center right away.

Tamper Evident: Sealed for your protection. Do not use if seal is broken or missing.

KEEP OUT OF REACH OF CHILDREN:

In case of overdose, contact a physician or Poison Control Center right away.

DIRECTIONS:

1-10 drops under the tongue, 3 times a day or as directed by a health professional. Consult a physician for use in children under 12 years of age.

INACTIVE INGREDIENTS:

Demineralized water, 25% ethanol

QUESTIONS:

Dist. By Deseret Biologicals, Inc.

469 W. Parkland Drive

Sandy, UT 84070

www.desbio.com

800-827-8204

PACKAGE LABEL DISPLAY:

Des Bio

Bladder Kidney

Meridian Opener

Homeopathic

NDC 43742-0836-1

1 FL OZ (30 ml)